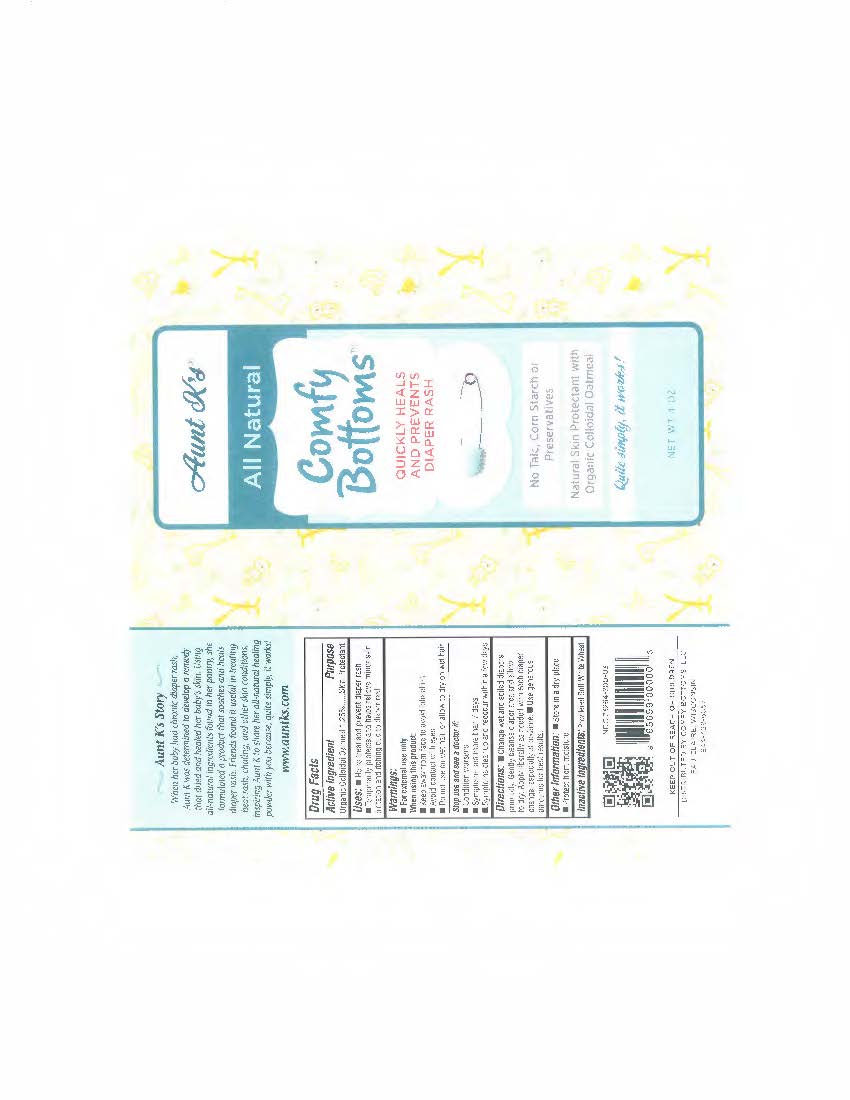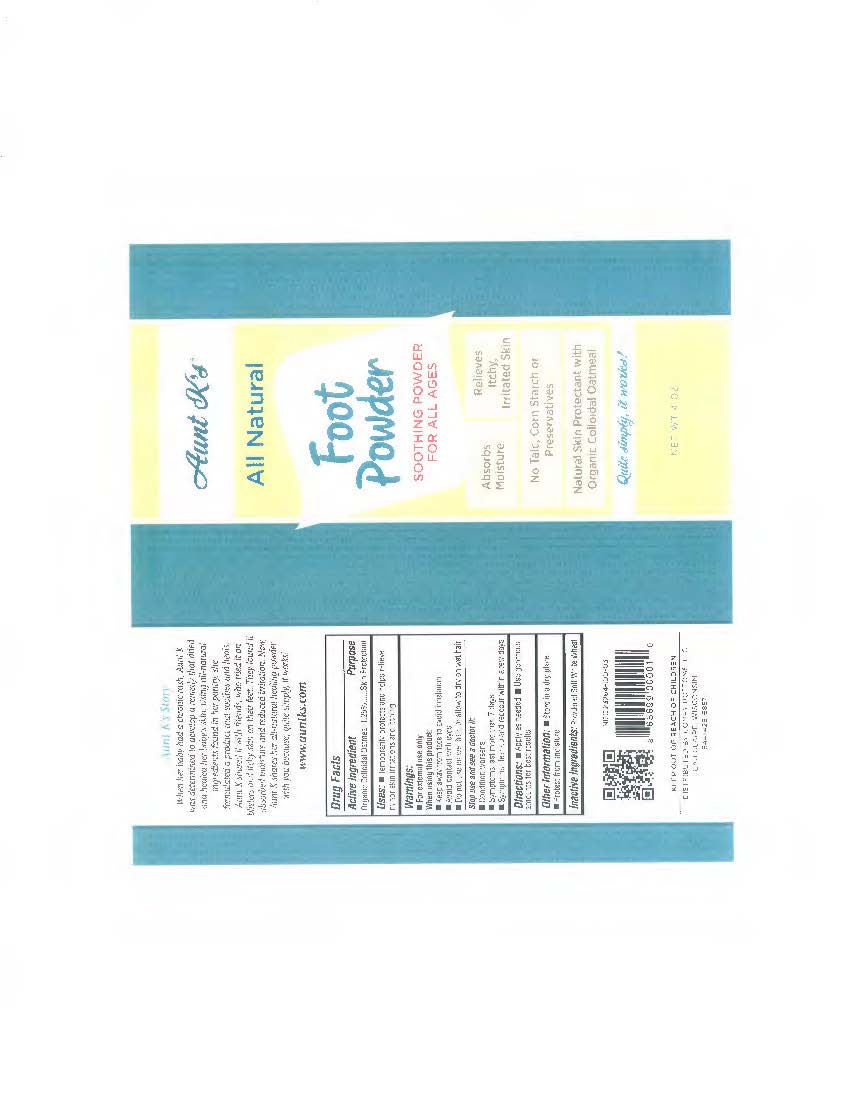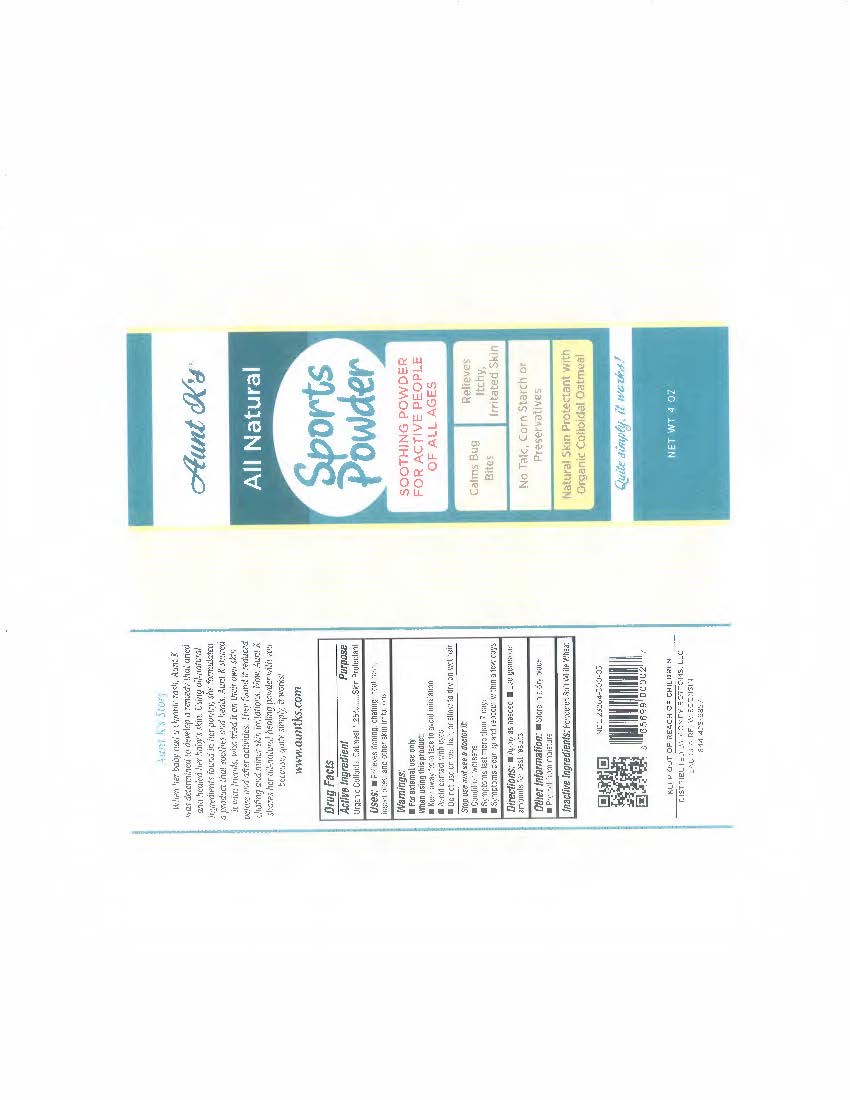 DRUG LABEL: Aunt Ks
NDC: 23264-200 | Form: POWDER
Manufacturer: Comfy Bottoms, LLC
Category: otc | Type: HUMAN OTC DRUG LABEL
Date: 20161229

ACTIVE INGREDIENTS: OATMEAL 1.25 g/100 g
INACTIVE INGREDIENTS: WHEAT

OTC- Active Ingredients Section

Organic Colloidal Oatmeal 1.25%..... Skin Protectant

Sto use and see a doctor if:

Conditions worsen

Symptoms last more than 7 days

Symptoms clear up and reoccur within a few days.

OTC- Warnings Section

For external use only

when using this product: Keep away from face to avoid inhalation

Avoid contact with eyes

Do not use on wet hair, or allow to dry on wet hair

Other information

Store in a dry place

protect from moisture

OTC- Purpose Section

Uses: Helps treat and prevent diaper rash

Temporarily protects and helps relieve minor skin irritation and itching due to diaper rash.

Inactive Ingredients

Powdered White Soft Wheat

Keep out of reach of Children

Dosage section

Apply as Needed

Use Generous amounts for best results

Indications and usage

Uses: Helps treat and prevent diaper rash